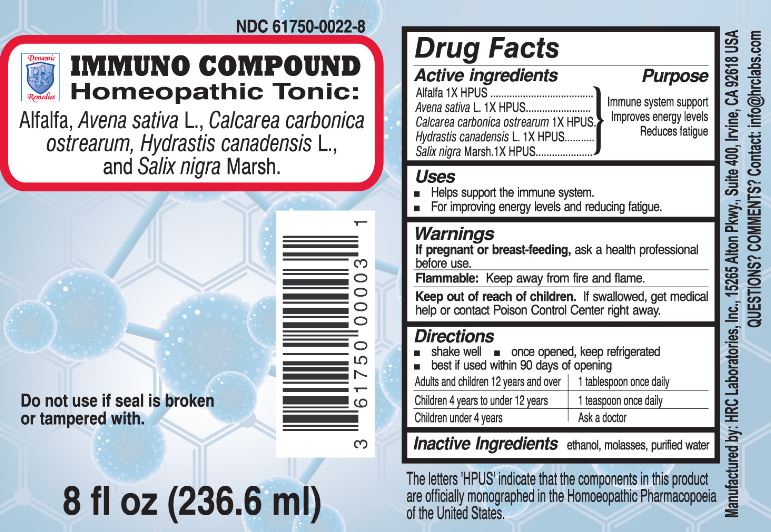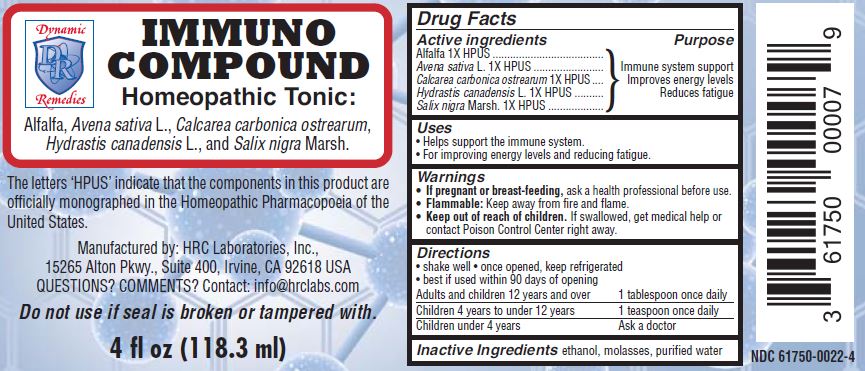 DRUG LABEL: Immuno Compound Homeopathic Tonic
NDC: 61750-0022 | Form: LIQUID
Manufacturer: HRC Laboratories, Inc.
Category: homeopathic | Type: HUMAN OTC DRUG LABEL
Date: 20180303

ACTIVE INGREDIENTS: ALFALFA 1 [hp_X]/236.6 mL; AVENA SATIVA FLOWERING TOP 1 [hp_X]/236.6 mL; OYSTER SHELL CALCIUM CARBONATE, CRUDE 1 [hp_X]/236.6 mL; GOLDENSEAL 1 [hp_X]/236.6 mL; SALIX NIGRA BARK 1 [hp_X]/236.6 mL
INACTIVE INGREDIENTS: ALCOHOL; WATER

Immuno Compound Homeopathic Tonic

Drug Facts

Active ingredients

Alfalfa 1X HPUS

Avena Sativa L. 1X HPUS

Calcarea carbonica ostrearum 1X HPUS

Hydrastis canadensis L. 1X HPUS

Salix nigra Marsh. 1X HPUS

Purpose

Immune system support

Improves energy levels

Reduces fatigue

Uses

- Helps support the immune system.
- For improving energy levels and reducing fatigue.

Warnings

PREGNANCY OR BREAST FEEDING

If pregnant or breast-feeding, ask a health professional before use.

STORAGE AND HANDLING

Flammable: Keep away from fire and flame.

Keep out of reach of children. If swallowed, get medical help or contact Poison Control Center right away.

Directions

- shake well
- once opened, keep refrigerated
- best if used within 90 days of opening

Adults and children 12 years and over | 1 tablespoon once daily
Children 4 years to under 12 years | 1 teaspoon once daily
Children under 4 years | Ask a doctor

Inactive Ingredients ethanol, molasses, purified water

The letters 'HPUS' indicate that the components in this product are officially monographed in the Homeopathic Pharmacopoeia of the United States.

Manufactured by: HRC Laboratories, 115265 Alton Pkwy, Ste 400, Irvine, CA 92618 USA
Questions Comments Contact info@hrclabs.com

Package Label - 8oz

NDC 61750-0022-8

IMMUNO COMPOUND

HOMEOPATHIC TONIC:

Alfalfa, Avena Sativa L., Calcarea carbonica ostrearum, Hydrastis canadensis L., and Salix nigra Marsh.

Do not use if seal is broken or tampered with.

8 fl oz (236.6 ml)

Package Lable - 4oz

NDC 61750-0022-4

IMMUNO COMPOUND

HOMEOPATHIC TONIC:

Alfalfa, Avena Sativa L., Calcarea carbonica ostrearum, Hydrastis canadensis L., and Salix nigra Marsh.

Do not use if seal is broken or tampered with.

4 fl oz (118.3 ml)